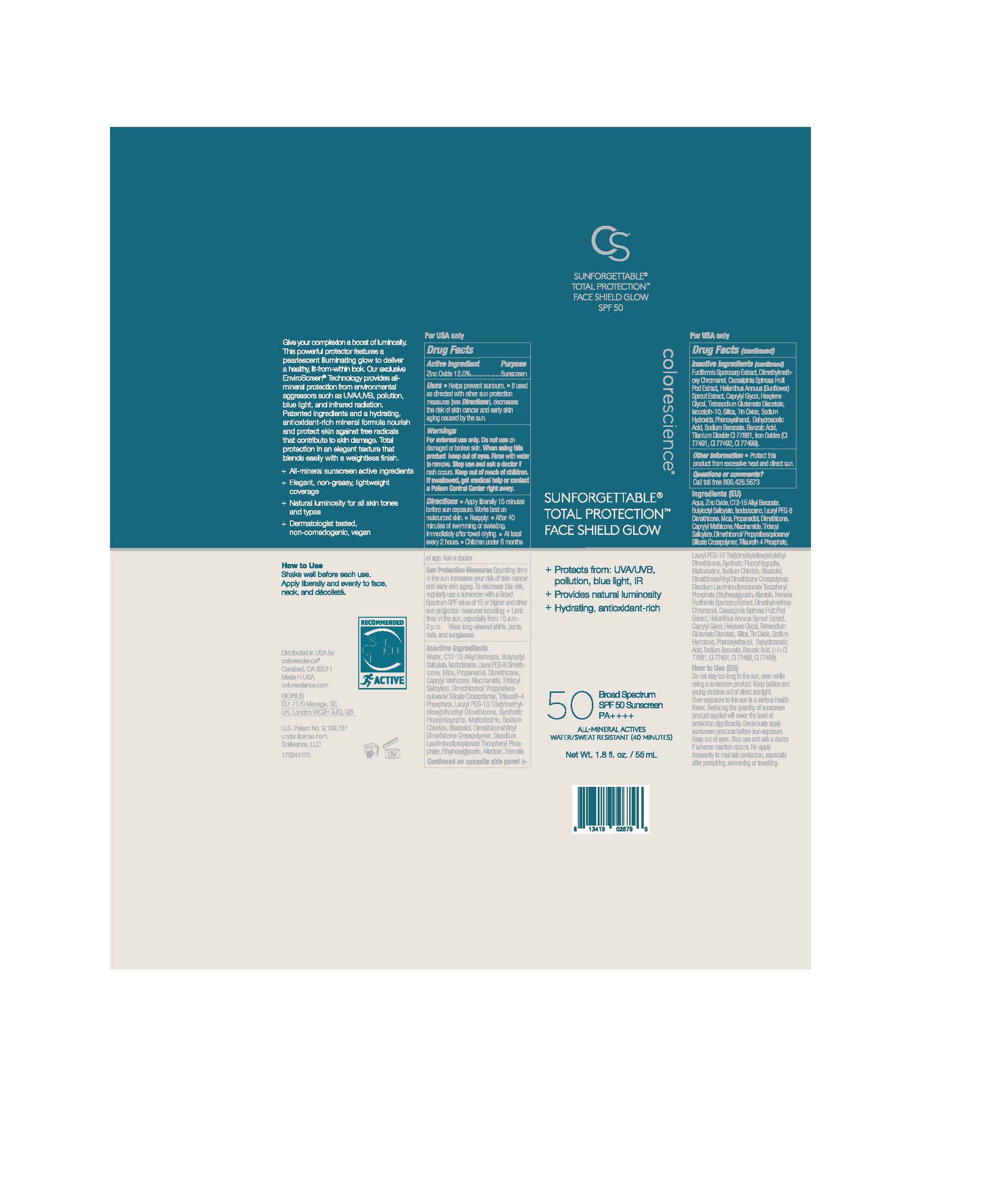 DRUG LABEL: Sunforgettable Total Protection Face Shield Glow
NDC: 68078-041 | Form: LOTION
Manufacturer: Colorescience
Category: otc | Type: HUMAN OTC DRUG LABEL
Date: 20251015

ACTIVE INGREDIENTS: ZINC OXIDE 135.6 mg/1 mL
INACTIVE INGREDIENTS: DISODIUM LAURIMINODIPROPIONATE TOCOPHERYL PHOSPHATES; TITANIUM DIOXIDE; DIMETHYLMETHOXY CHROMANOL; SILICON DIOXIDE; DIMETHICONE/VINYL DIMETHICONE CROSSPOLYMER (SOFT PARTICLE); ALLANTOIN; TRILAURETH-4 PHOSPHATE; BUTYLOCTYL SALICYLATE; ISODODECANE; CAPRYLYL GLYCOL; DEHYDROACETIC ACID; DIMETHICONE; HELIANTHUS ANNUUS SPROUT; MALTODEXTRIN; TOCOPHEROL; CAESALPINIA SPINOSA FRUIT POD; SODIUM HYDROXIDE; WATER; MICA; NIACINAMIDE; ETHYLHEXYLGLYCERIN; HEXYLENE GLYCOL; ALKYL (C12-15) BENZOATE; DIMETHICONOL/PROPYLSILSESQUIOXANE/SILICATE CROSSPOLYMER (450000000 MW); PROPANEDIOL; TETRASODIUM GLUTAMATE DIACETATE; SODIUM CHLORIDE; PHENOXYETHANOL; .ALPHA.-BISABOLOL, (+)-; TRIDECYL SALICYLATE

Sunforgettable Total Protection Face Shield Glow